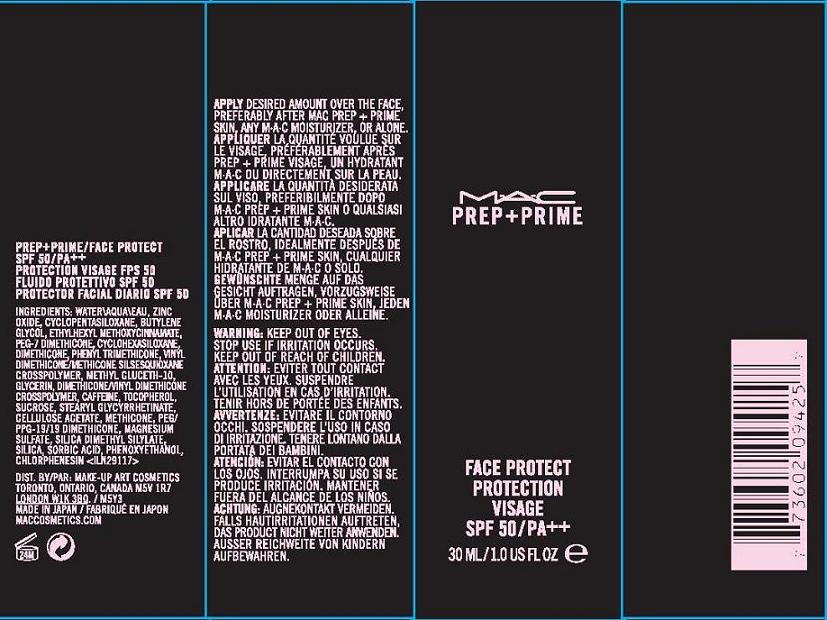 DRUG LABEL: PREP and PRIME FACE PROTECTION
NDC: 40046-0047 | Form: CREAM
Manufacturer: MAKEUP ART COSMETICS
Category: otc | Type: HUMAN OTC DRUG LABEL
Date: 20110916

ACTIVE INGREDIENTS: ZINC OXIDE 16.1 mL/100 mL; OCTINOXATE 7.5 mL/100 mL
INACTIVE INGREDIENTS: WATER; CYCLOMETHICONE 5; BUTYLENE GLYCOL; DIMETHICONE; CYCLOMETHICONE 6; PHENYL TRIMETHICONE; METHYL GLUCETH-10; GLYCERIN; CAFFEINE; ALPHA-TOCOPHEROL; SUCROSE; STEARYL GLYCYRRHETINATE; CELLULOSE ACETATE; MAGNESIUM SULFATE, UNSPECIFIED; SILICON DIOXIDE; SORBIC ACID; PHENOXYETHANOL; CHLORPHENESIN

ACTIVE INGREDIENT

ACTIVE INGREDIENTS: ZINC OXIDE 16.10% [] OCTINOXATE 7.50%

INACTIVE INGREDIENT

INACTIVE INGREDIENTS: WATER\AQUA\EAU [] CYCLOPENTASILOXANE [] BUTYLENE GLYCOL [] PEG-7 DIMETHICONE [] CYCLOHEXASILOXANE [] DIMETHICONE [] PHENYL TRIMETHICONE [] VINYL DIMETHICONE/METHICONE SILSESQUIOXANE CROSSPOLYMER [] METHYL GLUCETH-10 [] GLYCERIN [] DIMETHICONE/VINYL DIMETHICONE CROSSPOLYMER [] CAFFEINE [] TOCOPHEROL [] SUCROSE [] STEARYL GLYCYRRHETINATE [] CELLULOSE ACETATE [] METHICONE [] PEG/PPG-19/19 DIMETHICONE [] MAGNESIUM SULFATE [] SILICA DIMETHYL SILYLATE [] SILICA [] SORBIC ACID [] PHENOXYETHANOL [] CHLORPHENESIN

WARNINGS

WARNING: KEEP OUT OF EYES. STOP USE IF IRRITATION OCCURS. KEEP OUT OF REACH OF CHILDREN

PACKAGE LABEL

PRINCIPAL DISPLAY PANEL

MAC

PREP + PRIME

FACE PROTECT

PROTECTION

SPF 50

1 FL OZ/ 30 ML

makeup art cosmetics

toronto, canada